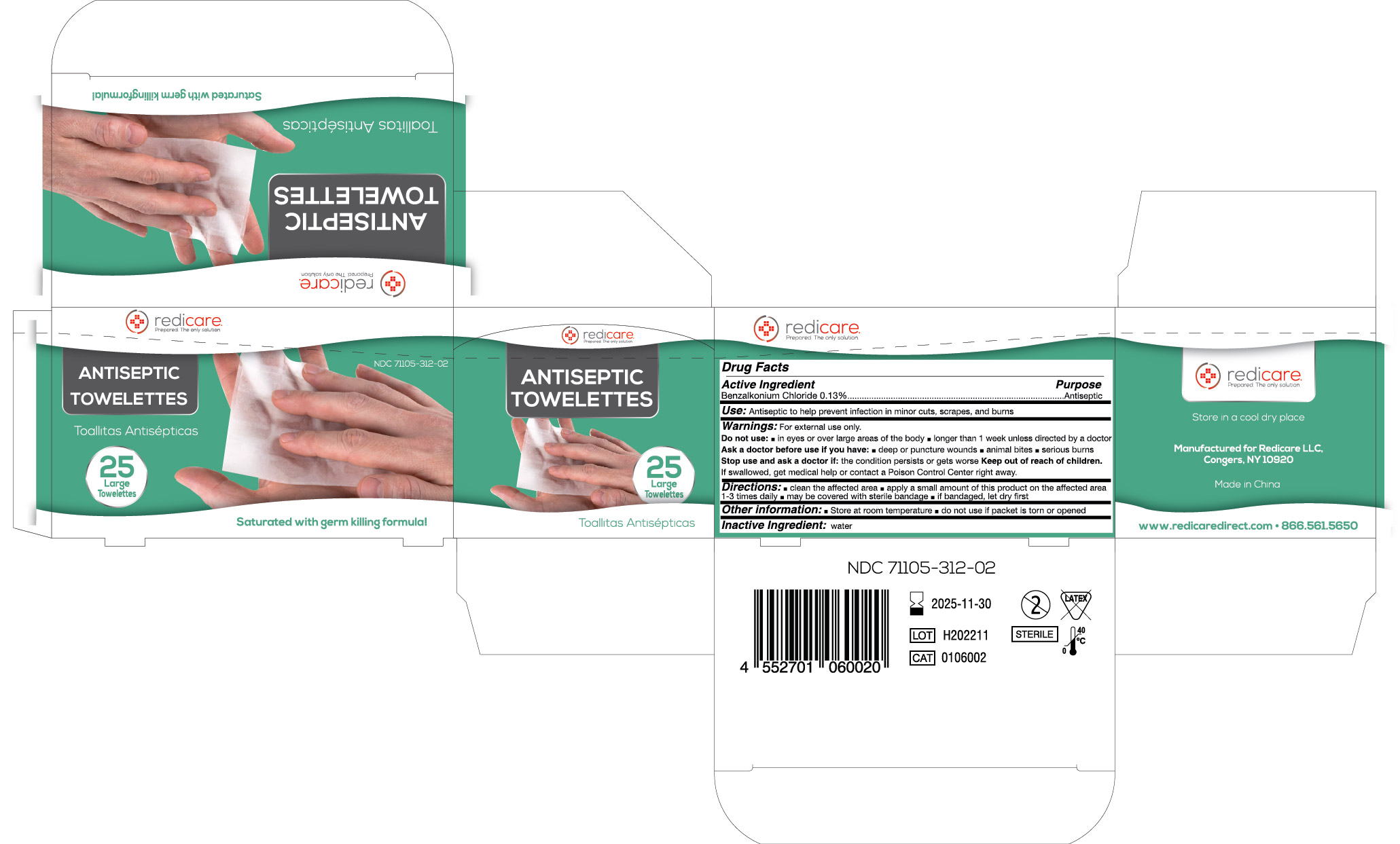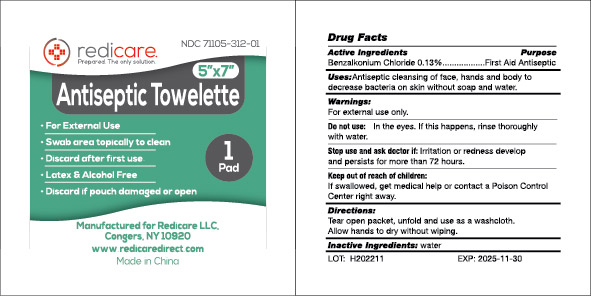 DRUG LABEL: Redicare Antiseptic Cleaning Towelettes
NDC: 71105-312 | Form: SWAB
Manufacturer: Redicare LLC
Category: otc | Type: HUMAN OTC DRUG LABEL
Date: 20250305

ACTIVE INGREDIENTS: BENZALKONIUM CHLORIDE 0.13 g/100 g
INACTIVE INGREDIENTS: WATER

BZK wipes 71105-312

Active Ingredient

Benzalkonium Chloride 0.13%

Purpose

Antiseptic

Use:

Antiseptic to help prevent infection in minor cuts, scrapes, and burns.

Warnings:

For external use only.

Do not use:

- in eyes or over large areas of the body
- longer than 1 week unless directed by a doctor

Ask a doctor before use if you have:

- deep or puncture wounds
- animal bites
- serious burns

Stop use and ask a doctor if:

the condition persists or gets worse

Keep out of reach of children.

If swallowed, get medical help or contact a Poison Control Center right away.

Directions:

- clean the affected area
- apply a small amount of this product on the affected area 1-3 times daily
- may be covered with a sterile bandage
- If bandaged, let dry first

Other information:

- Store at room temperature
- Do not use if packet is torn or opened

Inactive ingredient:

water